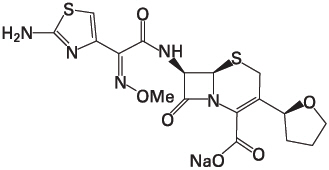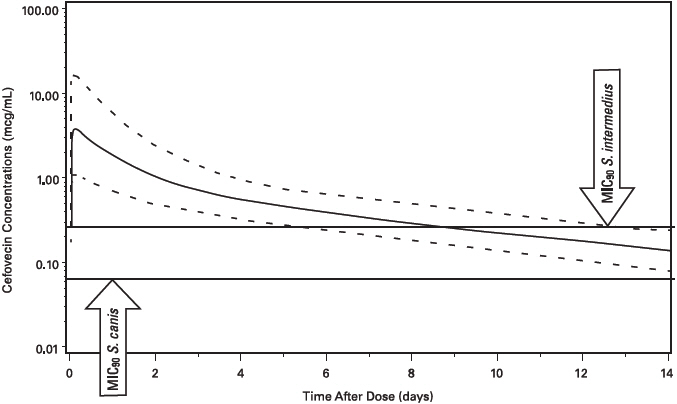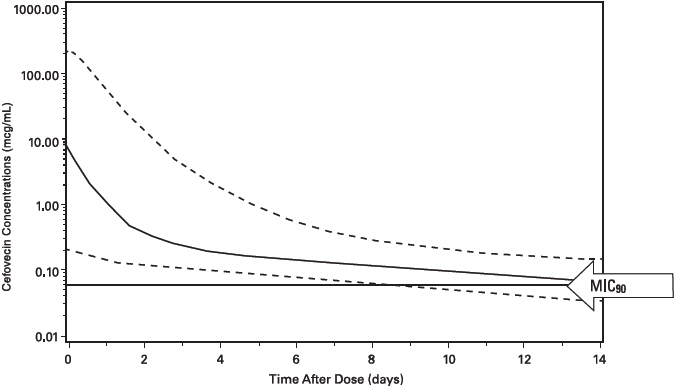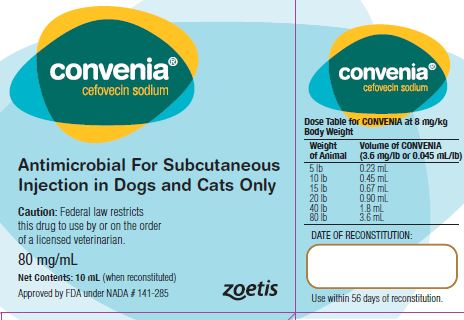 DRUG LABEL: Convenia
NDC: 54771-1520 | Form: INJECTION, POWDER, LYOPHILIZED, FOR SOLUTION
Manufacturer: Zoetis Inc.
Category: animal | Type: PRESCRIPTION ANIMAL DRUG LABEL
Date: 20221208

ACTIVE INGREDIENTS: CEFOVECIN SODIUM 80 mg/1 mL
INACTIVE INGREDIENTS: METHYLPARABEN 1.8 mg/1 mL; PROPYLPARABEN 0.2 mg/1 mL; SODIUM CITRATE 5.8 mg/1 mL; CITRIC ACID MONOHYDRATE 0.1 mg/1 mL; SODIUM HYDROXIDE; HYDROCHLORIC ACID

convenia®

convenia®
(cefovecin sodium)
Antimicrobial for Subcutaneous Injection in Dogs and Cats Only

CAUTION

Federal law restricts this drug to use by or on the order of a licensed veterinarian.

DESCRIPTION

Cefovecin sodium is a semi-synthetic broad-spectrum antibacterial agent from the cephalosporin class of chemotherapeutic agents. Cefovecin is the non-proprietary designation for (6R,7R)-7-[[(2Z)-(2-amino-4-thiazolyl)(methoxyimino)acetyl]amino]-8-oxo-3-[(2S)-tetrahydro-2-furanyl]-5-thia-1-azabicyclo[4.2.0]oct-2-ene-2-carboxylic acid, monosodium salt.

Figure 1: Chemical structure of cefovecin sodium.

Each mL of CONVENIA reconstituted lyophile contains cefovecin sodium equivalent to 80.0 mg cefovecin, methylparaben 1.8 mg (preservative), propylparaben 0.2 mg (preservative), sodium citrate dihydrate 5.8 mg and citric acid monohydrate 0.1 mg, sodium hydroxide or hydrochloric acid as required to adjust pH.

INDICATIONS

Dogs

CONVENIA is indicated for the treatment of skin infections (secondary superficial pyoderma, abscesses, and wounds) in dogs caused by susceptible strains of Staphylococcus intermedius and Streptococcus canis (Group G).

Cats

CONVENIA is indicated for the treatment of skin infections (wounds and abscesses) in cats caused by susceptible strains of Pasteurella multocida.

DOSAGE AND ADMINISTRATION

Dogs

CONVENIA should be administered as a single subcutaneous injection of 3.6 mg/lb (8 mg/kg) body weight. A second subcutaneous injection of 3.6 mg/lb (8 mg/kg) may be administered if response to therapy is not complete. The decision for a second injection for any individual dog should take into consideration such factors as progress toward clinical resolution, the susceptibility of the causative organisms, and the integrity of the dog's host-defense mechanisms. Therapeutic drug concentrations after the first injection are maintained for 7 days for S. intermedius infections and for 14 days for S. canis (Group G) infections. Maximum treatment should not exceed 2 injections.

Cats

CONVENIA should be administered as a single, one-time subcutaneous injection at a dose of 3.6 mg/lb (8 mg/kg) body weight. After an injection of CONVENIA, therapeutic concentrations are maintained for approximately 7 days for Pasteurella multocida infections.

General Dosing Information

A sample of the lesion should be obtained for culture and susceptibility testing prior to beginning antimicrobial therapy. Once results become available, continue with appropriate therapy. If acceptable response to treatment is not observed, or if no improvement is seen within 3 to 4 days, then the diagnosis should be re-evaluated and appropriate alternative therapy considered.

CONVENIA may persist in the body for up to 65 days. The effect of remaining concentrations of cefovecin on any subsequent antimicrobial therapies has not been determined. Fluoroquinolone and aminoglycoside antimicrobials have been reported to be compatible with cephalosporin antimicrobial agents.^1,2,3

Table 1: Dose Table for CONVENIA at 8 mg/kg Body Weight
Weight of Animal | Volume of CONVENIA (3.6 mg/lb or 0.045 mL/lb)
5 lb | 0.23 mL
10 lb | 0.45 mL
15 lb | 0.67 mL
20 lb | 0.90 mL
40 lb | 1.8 mL
80 lb | 3.6 mL

PREPARATION OF SOLUTION FOR INJECTION: To deliver the appropriate dose, aseptically reconstitute CONVENIA with 10 mL Sterile Water for Injection. Shake and allow vial to sit until all material is visually dissolved. The resulting solution contains cefovecin sodium equivalent to 80 mg/mL cefovecin. CONVENIA is light sensitive. The vial should be stored in the original carton and refrigerated when not in use. Use the entire contents of the vial within 56 days of reconstitution.

CONTRAINDICATIONS

CONVENIA is contraindicated in dogs and cats with known allergy to cefovecin or to β-lactam (penicillins and cephalosporins) group antimicrobials. Anaphylaxis has been reported with the use of this product in foreign market experience. If an allergic reaction or anaphylaxis occurs, CONVENIA should not be administered again and appropriate therapy should be instituted. Anaphylaxis may require treatment with epinephrine and other emergency measures, including oxygen, intravenous fluids, intravenous antihistamine, corticosteroids, and airway management, as clinically indicated. Adverse reactions may require prolonged treatment due to the prolonged systemic drug clearance (65 days).

WARNINGS

Not for use in humans. Keep this and all drugs out of reach of children. Consult a physician in case of accidental human exposure. For subcutaneous use in dogs and cats only. Antimicrobial drugs, including penicillins and cephalosporins, can cause allergic reactions in sensitized individuals. To minimize the possibility of allergic reactions, those handling such antimicrobials, including cefovecin, are advised to avoid direct contact of the product with the skin and mucous membranes.

PRECAUTIONS

Prescribing antibacterial drugs in the absence of a proven or strongly suspected bacterial infection is unlikely to provide benefit to treated animals and may increase the risk of the development of drug-resistant animal pathogens.

The safe use of CONVENIA in dogs or cats less than 4 months of age (see Animal Safety) and in breeding or lactating animals has not been determined. Safety has not been established for IM or IV administration. The long-term effects on injection sites have not been determined. CONVENIA is slowly eliminated from the body, approximately 65 days is needed to eliminate 97% of the administered dose from the body. Animals experiencing an adverse reaction may need to be monitored for this duration.

CONVENIA has been shown in an experimental in vitro system to result in an increase in free concentrations of carprofen, furosemide, doxycycline and ketoconazole. Concurrent use of these or other drugs that have a high degree of protein-binding (e.g. NSAIDs, propofol, cardiac, anticonvulsant, and behavioral medications) may compete with cefovecin binding and cause adverse reactions.

Positive direct Coombs' test results and false positive reactions for glucose in the urine have been reported during treatment with some cephalosporin antimicrobials. Cephalosporin antimicrobials may also cause falsely elevated urine protein determinations. Some antimicrobials, including cephalosporins, can cause lowered albumin values due to interference with certain testing methods.

Occasionally, cephalosporins and NSAIDs have been associated with myelotoxicity, thereby creating a toxic neutropenia^4. Other hematological reactions seen with cephalosporins include neutropenia, anemia, hypoprothrombinemia, thrombocytopenia, prolonged prothrombin time (PT) and partial thromboplastin time (PTT), platelet dysfunction and transient increases in serum aminotransferases.

ADVERSE REACTIONS

Dogs

A total of 320 dogs, ranging in age from 8 weeks to 19 years, were included in a field study safety analysis. Adverse reactions reported in dogs treated with CONVENIA and the active control are summarized in Table 2.

Table 2: Number of Dogs [Some dogs may have experienced more than one adverse reaction or more than one occurrence of the same adverse reaction during the study.] with Adverse Reactions Reported During the Field Study with CONVENIA
Adverse Reaction | CONVENIA (n=157) | Active Control (n=163)
Lethargy | 2 | 7
Anorexia/Decreased Appetite | 5 | 8
Vomiting | 6 | 12
Diarrhea | 6 | 7
Blood in Feces | 1 | 2
Dehydration | 0 | 1
Flatulence | 1 | 0
Increased Borborygmi | 1 | 0

Mild to moderate elevations in serum gamma glutamyl transferase or serum alanine aminotransferase were noted post-treatment in several of the CONVENIA-treated dogs. No clinical abnormalities were noted with these findings.

One CONVENIA-treated dog in a separate field study experienced diarrhea post-treatment lasting four weeks. The diarrhea resolved.

Cats

A total of 291 cats, ranging in age from 2.4 months (one cat) to 21 years, were included in the field study safety analysis. Adverse reactions reported in cats treated with CONVENIA and the active control are summarized in Table 3.

Table 3: Number of Cats [Some cats may have experienced more than one adverse reaction or more than one occurrence of the same adverse reaction during the study.] with Adverse Reactions Reported During the Field Study with CONVENIA.
Adverse Reaction | CONVENIA (n=147) | Active Control (n=144)
Vomiting | 10 | 14
Diarrhea | 7 | 26
Anorexia/Decreased Appetite | 6 | 6
Lethargy | 6 | 6
Hyper/Acting Strange | 1 | 1
Inappropriate Urination | 1 | 0

Four CONVENIA cases had mildly elevated post-study ALT (one case was elevated pre-study). No clinical abnormalities were noted with these findings.

Twenty-four CONVENIA cases had normal pre-study BUN values and elevated poststudy BUN values (37 – 39 mg/dL post-study). There were 6 CONVENIA cases with normal pre- and mildly to moderately elevated post-study creatinine values. Two of these cases also had an elevated post-study BUN. No clinical abnormalities were noted with these findings.

One CONVENIA-treated cat in a separate field study experienced diarrhea post-treatment lasting 42 days. The diarrhea resolved.

FOREIGN MARKET EXPERIENCE: The following adverse events were reported voluntarily during post-approval use of the product in dogs and cats in foreign markets: death, tremors/ataxia, seizures, anaphylaxis, acute pulmonary edema, facial edema, injection site reactions (alopecia, scabs, necrosis, and erythema), hemolytic anemia, salivation, pruritus, lethargy, vomiting, diarrhea, and inappetance.

CONTACT INFORMATION

For a copy of the Safety Data Sheet or to report adverse reactions, call Zoetis Inc. at 1-888-963-8471. For additional information about adverse drug experience reporting for animal drugs, contact FDA at 1-888-FDA-VETS or at www.fda.gov/reportanimalae.

CLINICAL PHARMACOLOGY

Pharmacokinetics

Cefovecin is rapidly and completely absorbed following subcutaneous administration. Non-linear kinetics is exhibited (plasma concentrations do not increase proportionally with dose). Cefovecin does not undergo hepatic metabolism and the majority of a dose is excreted unchanged in the urine. Elimination also occurs from excretion of unchanged drug in the bile. Cefovecin is a highly protein bound molecule in dog plasma (98.5%) and cat plasma (99.8%) and may compete with other highly protein bound drugs for plasma protein binding sites that could result in transient, higher free drug concentrations of either compound. Pharmacokinetic parameters following subcutaneous dosing at 8 mg/kg in the dog and cat are summarized in Table 4.

Table 4: Pharmacokinetic Parameters Reflecting Total Drug Concentrations in Plasma (mean ± standard deviation or range) Following an 8 mg/kg Intravenous or Subcutaneous Dose of Cefovecin in Dogs and Cats
PARAMETER | MEAN ± SD [SD = standard deviation] or (Range)
PARAMETER | Dogs | Cats [= a phase effect was observed, only data for the first phase are provided (n=6); all other data provided are derived from 12 animals]
Terminal plasma elimination half-life, T1/2 (h) [= SC] [= harmonic mean] | 133 ± 16 | 166 ± 18
AUC0-inf (μg∙h/mL) [= geometric mean] | 10400 ± 1900 | 22700 ± 3450
Time of maximum concentration, Tmax (h) | 6.2 (0.5-12.0) | 2.0 (0.5-6.0)
Maximum concentration, Cmax (μg/mL) [= arithmetic mean] | 121 ± 51 | 141 ± 12
Vdss (L/kg) [= IV] | 0.122 ± 0.011 | 0.090 ± 0.010
CLtotal (mL/h/kg) | 0.76 ± 0.13 | 0.350 ± 0.40

Population Pharmacokinetics

Dogs

Cefovecin plasma concentrations in the dog have been characterized by the use of population pharmacokinetic (PPK) data. Plasma cefovecin concentration data were pooled from seven laboratory pharmacokinetic studies, each involving young, normal healthy Beagle dogs. The final dataset contained 591 concentration records from 39 dogs. The simulations from the model provide the mean population estimate and the 5th and 95th percentile of the population estimates of total and free cefovecin concentrations over time. Figure 2 shows the predicted free plasma concentrations following administration of 8 mg/kg body weight to dogs. Based upon these predicted concentrations, 95% of the canine population will have active (free) drug concentrations > the MIC90 of S. canis (0.06 µg/mL) for approximately 14 days and free concentrations > the MIC90 for S. intermedius (0.25 μg/mL) for approximately 7 days following a single 8 mg/kg subcutaneous injection of cefovecin. (See MICROBIOLOGY.)

Figure 2: Population Predicted Free Concentration of Cefovecin in Plasma Following a Single Subcutaneous Injection of 8 mg/kg Body Weight in Dogs (solid line is population prediction, dotted lines are the 5th and 95th percentiles for the population prediction).

Cats

Cefovecin plasma concentrations in the cat have been characterized by the use of PPK data. Plasma cefovecin concentration data were pooled from four laboratory pharmacokinetic studies. The final dataset contained 338 concentration records from 22 cats. The simulations from the model provide the mean population estimate as well as the 5th and 95th percentile of the population estimates of total and free cefovecin concentrations over time. Figure 3 displays the predicted free plasma concentrations following administration of 8 mg/kg body weight to cats. Based upon these predicted concentrations, 95% of the feline population will have active (free) drug concentrations > the MIC90 of Pasteurella multocida (0.06 µg/mL) for approximately 7 days when administered a single 8 mg/kg subcutaneous injection of cefovecin. (See MICROBIOLOGY.)

Figure 3: Population Predicted Free Concentration of Cefovecin in Plasma Following a Single Subcutaneous Injection of 8 mg/kg Body Weight in Cats (solid line is population prediction, dotted lines are the 5th and 95th percentiles for the population prediction).

MICROBIOLOGY

MICROBIOLOGY: CONVENIA is a cephalosporin antibiotic. Like other β-lactam antimicrobials, CONVENIA exerts its inhibitory effect by interfering with bacterial cell wall synthesis. This interference is primarily due to its covalent binding to the penicillin-binding proteins (PBPs) (i.e., transpeptidase and carboxypeptidase), which are essential for synthesis of the bacterial cell wall. For E. coli, the in vitro activity of CONVENIA is comparable to other cephalosporins, but due to the high-affinity protein-binding, the in vivo free concentration of cefovecin does not reach the MIC90 for E. coli (1.0 μg/mL). CONVENIA is not active against Pseudomonas spp. or enterococci.

Dogs

The minimum inhibitory concentration (MIC) values for cefovecin against label-claim pathogens isolated from skin infections in dogs enrolled in a 2001-2003 field effectiveness study are presented in Table 5. All MICs were determined in accordance with the Clinical and Laboratory Standards Institute (CLSI) standards.

Table 5. Activity of CONVENIA Against Pathogens Isolated from Dogs Treated With CONVENIA in Field Studies in the U.S. During 2001-2003.
Disease | Pathogen | Microbiological Treatment Outcome | Number of Isolates | Sample Collection (Time Relative to Treatment) | MIC50 µg/mL | MIC90 µg/mL | MIC Range µg/mL
Skin infections | Staphylococcus intermedius | Success | 44 | Pre-Treatment | 0.12 | 0.25 | ≤ 0.06 - 2
Skin infections | Staphylococcus intermedius | Failure | 4 | Pre-Treatment |  |  | 0.12 - 2
Skin infections | Streptococcus canis (Group G) | Success | 16 | Pre-Treatment | ≤ 0.06 | ≤ 0.06 | ≤ 0.06
Skin infections | Streptococcus canis (Group G) | Failure | 2 | Pre-Treatment |  |  | ≤ 0.06

Cats

The MIC values for cefovecin against Pasteurella multocida isolated from skin infections (wounds and abscesses) in cats enrolled in a 2001-2003 field effectiveness study are presented in Table 6. All MICs were determined in accordance with the CLSI standards.

Table 6. Activity of CONVENIA Against Pathogens Isolated from Cats Treated With CONVENIA in Field Studies in the U.S. During 2001-2003.
Disease | Pathogen | Microbiological Treatment Outcome | Number of Isolates | Sample Collection (Time Relative to Treatment) | MIC50 µg/mL | MIC90 µg/mL | MIC Range µg/mL
Skin infections | Pasteurella multocida | Success | 57 | Pre-Treatment | ≤ 0.06 | ≤ 0.06 | ≤ 0.06 -0.12
Skin infections | Pasteurella multocida | Failure | 1 | Pre-Treatment |  |  | ≤ 0.06

EFFECTIVENESS

Dogs

In a double-masked, 1:1 randomized canine field study conducted in the United States, the effectiveness of CONVENIA was compared to a cephalosporin active control. In this study, 320 dogs with superficial secondary pyoderma, abscesses, or infected wounds were treated with either a single injection of CONVENIA (n = 157) at 3.6 mg/lb (8 mg/kg) body weight or with an oral active control antibiotic (n = 163), administered twice daily for 14 days. In this study, dogs could receive a second course of therapy 14 days after the initial treatment. Of the 320 enrolled dogs, 22 of 157 dogs received two treatments of CONVENIA and 35 of 163 dogs received two courses of treatment with the active control. In the study, 118 of the 157 enrolled cases were evaluable for effectiveness for CONVENIA, and 117 of the 163 enrolled cases were evaluable for effectiveness of the active control antibiotic. CONVENIA was non-inferior to the active control. Table 7 summarizes the clinical success rates obtained 28 days after the initiation of the final course of therapy.

Table 7: Clinical Success Rates by Treatment Group 28 Days after the Initiation of the Final Course of Therapy.
Type of Infection | Dogs
Type of Infection | CONVENIA (n=118) | Active Control (n=117)
Skin (secondary superficial pyoderma, abscesses, and infected wounds) | 109 (92.4%) | 108 (92.3%)

CONVENIA was administered concomitantly with other commonly used veterinary products such as heartworm preventatives, flea control products, sedatives/tranquilizers, anesthetic agents, routine immunizations, antihistamines, thyroid hormone supplementation, and non-steroidal anti-inflammatory drugs during the field study.

Cats

In a double-masked, 1:1 randomized cat field study conducted in the United States, the effectiveness of CONVENIA was compared to an active control. In this study, 291 cats with infected wounds or abscesses were treated with either a single injection of CONVENIA (n = 147) at 3.6 mg/lb (8 mg/kg) body weight or with an oral active control antibiotic (n = 144), administered once daily for 14 days. CONVENIA was non-inferior to the active control. The clinical success rates were obtained 28 days after the initiation of therapy and are presented in Table 8.

Table 8: Clinical Success Rates by Treatment Group 28 Days after the Initiation of Therapy.
Type of Infection | Cats
Type of Infection | CONVENIA (n=89) | Active Control (n=88)
Skin (wounds and abscesses) | 86 (96.6%) | 80 (90.9%)

CONVENIA was used concomitantly with other commonly used veterinary products such as heartworm preventatives, flea control products, sedatives/tranquilizers, anesthetic agents, and vaccines during the field study.

ANIMAL SAFETY

Dogs

CONVENIA administered to healthy four month old dogs at doses of 12 mg/kg (1.5 ×), 36 mg/kg (4.5 ×), and 60 mg/kg (7.5 ×) every seven days by dorsoscapular subcutaneous injections was well-tolerated for a total of 5 doses. Vomiting and diarrhea were seen in all treatment groups, with the incidence of vomiting and the incidence and duration of diarrhea increasing in a dose-related manner. Injection site irritation and transient edema occurred with increasing frequency in a dose-related manner and with repeat injections. Two injection site reactions included a seroma over the shoulder and swelling lasting > 30 days. Dogs dosed at 36 mg/kg had a significant (p = 0.0088) increase in BUN (all means remained within the normal range) compared to the controls. One dog dosed at 60 mg/kg exhibited a glomerulopathy on histopathology, and one dog in this same group had minimal peliosis hepatis.

At an exaggerated dose of 180 mg/kg (22.5×) in dogs, CONVENIA caused some injection site irritation, vocalization and edema. Edema resolved within 8-24 hours.

Cats

CONVENIA administered to healthy four month old cats at doses of 12 mg/kg (1.5 ×), 36 mg/kg (4.5 ×), and 60 mg/kg (7.5 ×) every seven days by dorsoscapular subcutaneous injections was well tolerated for a total of 5 doses. Vomiting and diarrhea were observed in cats, with the incidence of vomiting, and the incidence and duration of diarrhea increasing in a dose-related manner. The mean albumin values for all the CONVENIA-treated cats were significantly lower (p ≤ 0.05) than the control values (all means remained within the normal range) for all time periods. The mean alkaline phosphatase values in the 60 mg/kg group were significantly higher (p ≤ 0.0291) than the control values for all time periods. Injection-site irritation and transient edema occurred with increasing frequency in a dose-related manner and with repeat injections. One cat in the 12 mg/kg group had a mild renal tubular and interstitial fibrosis, and one cat in the 12 mg/kg group had mild glomerulosclerosis on histopathology.

At an exaggerated dose of 180 mg/kg (22.5×), CONVENIA was associated with injection site irritation, vocalization and edema. Edema resolved within 8-24 hours. On Day 10, cats had lower mean white blood cell counts compared to the controls. One cat had a small amount of bilirubinuria on Day 10.

STORAGE INFORMATION

Store the powder and the reconstituted product in the original carton, refrigerated at 2° to 8° C (36° to 46° F). Use the entire contents of the vial within 56 days of reconstitution. PROTECT FROM LIGHT. After each use it is important to return the unused portion back to the refrigerator in the original carton. As with other cephalosporins, the color of the solution may vary from clear to amber at reconstitution and may darken over time. If stored as recommended, solution color does not adversely affect potency.

HOW SUPPLIED

CONVENIA is available as a 10 mL multi-use vial containing 800 milligrams of cefovecin as a lyophilized cake.

REFERENCES

^1Pillai SK, Moellering RC, and Eliopoulos GM. 2005. Antimicrobial combinations, pp 365-440. In V. Lorian (ed.) Antibiotics in Laboratory Medicine, 5th ed., Lippincott, Williams, and Wilkins, Philadelphia, PA.

^2Fish DN, Choi MK, and Jung R: Synergic activity of cephalosporins plus fluoroquinolones against Pseudomonas aeruginosa with resistance to one or both drugs. Journal of Antimicrobial Chemotherapy (2002) 50, 1045–1049.

^3Mayer I and Nagy E: Investigation of the synergic effects of aminoglycoside-fluoroquinolone and third-generation cephalosporin combinations against clinical isolates of Pseudomonas spp. Journal of Antimicrobial Chemotherapy (1999) 43, 651–657.

^4Birchard SJ and Sherding RG. Saunders Manual of Small Animal Practice, 2nd edition. W.B. Saunders Co. 2000: p. 166.

Approved by FDA under NADA # 141-285
zoetis
Distributed by:
Zoetis Inc.
Kalamazoo, MI 49007
Revised: July 2022
40039675